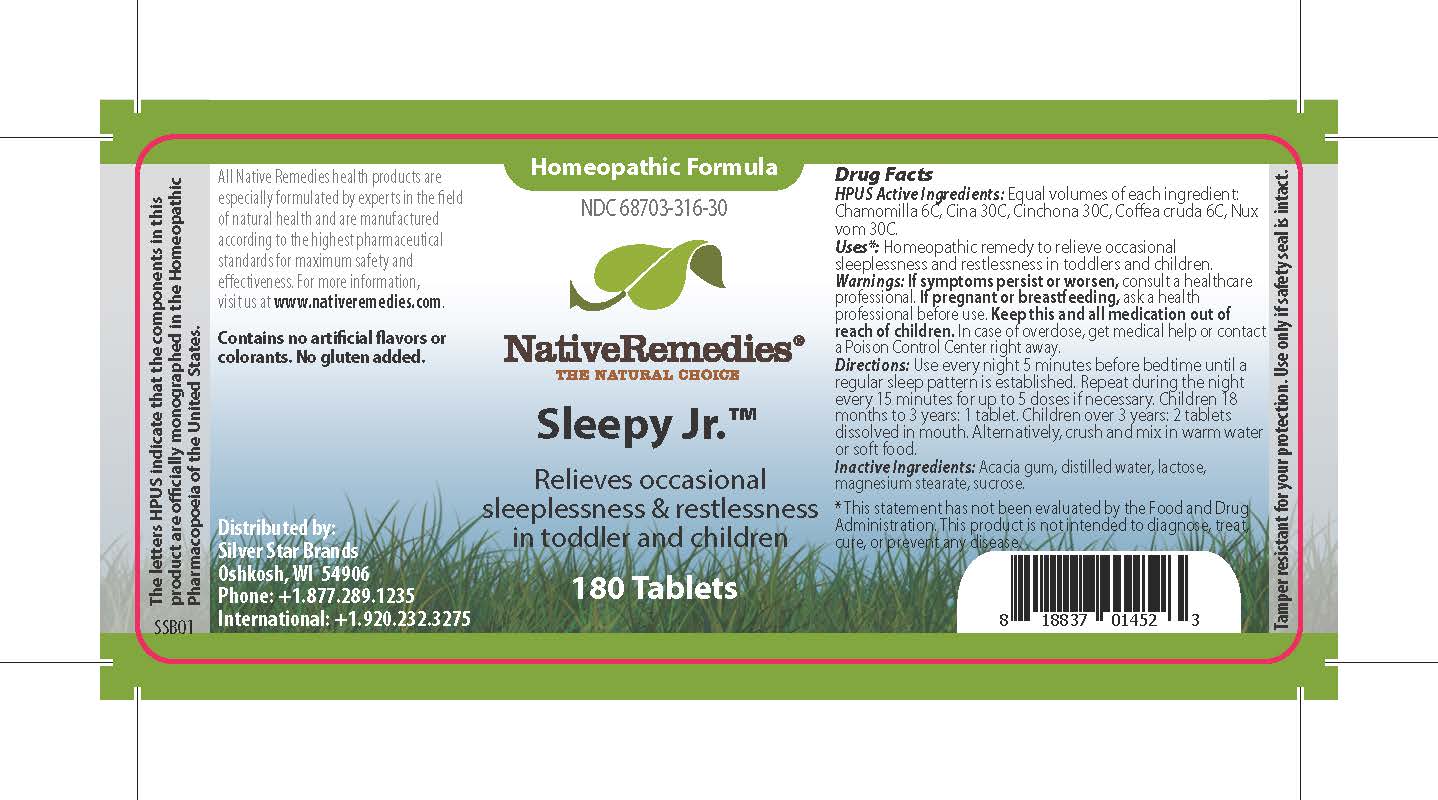 DRUG LABEL: Sleepy Jr
NDC: 68703-316 | Form: TABLET
Manufacturer: Silver Star Brands
Category: homeopathic | Type: HUMAN OTC DRUG LABEL
Date: 20241203

ACTIVE INGREDIENTS: STRYCHNOS NUX-VOMICA SEED 30 [hp_C]/1 1; MATRICARIA CHAMOMILLA FLOWERING TOP OIL 6 [hp_C]/1 1; ARTEMISIA CINA FLOWER 30 [hp_C]/1 1; COFFEA ARABICA FRUIT 6 [hp_C]/1 1; CINCHONA OFFICINALIS BARK 30 [hp_C]/1 1
INACTIVE INGREDIENTS: WATER; LACTOSE, UNSPECIFIED FORM; ACACIA; MAGNESIUM STEARATE; SUCROSE

NativeRemedies® Sleepy Jr.™

HPUS Active Ingredients: Equal volumes of each ingredient: Charmomilla 6C, Cina 30C, Cinchona 30C, Coffea cruda 6C, Nux vom 30C.

The letters HPUS indicate that the components in this product are officially monographed in the Homeopathic Pharmacopoeia of the United States.

Uses*

Uses*: Homeopathic remedy to relieve occasional sleeplessness and restlessness in toddlers and children.

*This statement has not been evaluated by the Food and Drug Administration. This product is not intended to diagnose, treat, cure, or prevent any disease.

Warnings

Warnings: If symptoms persist or worsen, consult a healthcare professional. If pregnant or breastfeeding, ask a health professional before use. Keep this and all medication out of reach of children. In case of overdose, get medical help or contact a Poison Control Center right away.

Directions

Directions: Use every night 5 minutes before bedtime until a regular sleep pattern is established. Repeat during the night every 15 minutes for up to 5 doses if necessary. Children 18 months to 3 years: 1 tablet. Children over 3 years: 2 tablets dissolved in mouth. Alternatively, crush and mix in warm water or soft food.

OTHER SAFETY INFORMATION

Contains no artificial flavors or colorants. No gluten added.

Tamper resistant for your protection. Use only if safety seals intact.

Inactive Ingredients

Inactive Ingredients: Acacia gum, distilled water, lactose, magnesium stearate, sucrose.

KEEP OUT OF REACH OF CHILDREN

Keep this and all medication out of reach of children.

PREGNANCY OR BREAST FEEDING

If pregnant or breastfeeding, ask a health professional before use.

PURPOSE

Relieves occasional sleeplessness & restlessness in toddler and children.